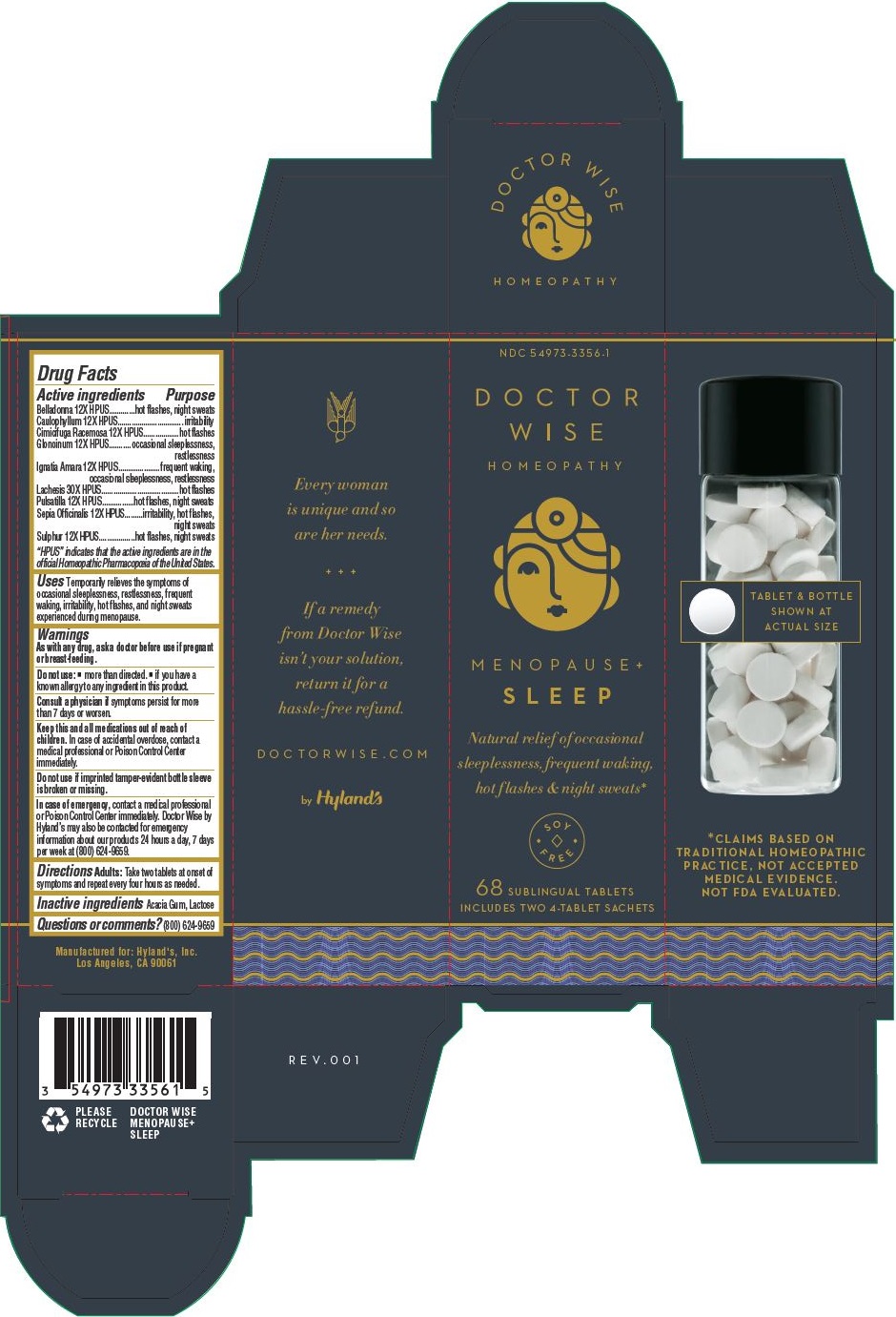 DRUG LABEL: Menopause Plus Sleep
NDC: 54973-3356 | Form: KIT | Route: SUBLINGUAL
Manufacturer: Hyland's Inc.
Category: homeopathic | Type: HUMAN OTC DRUG LABEL
Date: 20221213

ACTIVE INGREDIENTS: STRYCHNOS IGNATII SEED 12 [hp_X]/1 1; ATROPA BELLADONNA 12 [hp_X]/1 1; SEPIA OFFICINALIS JUICE 12 [hp_X]/1 1; SULFUR 12 [hp_X]/1 1; ANEMONE PULSATILLA 12 [hp_X]/1 1; CAULOPHYLLUM THALICTROIDES ROOT 12 [hp_X]/1 1; BLACK COHOSH 12 [hp_X]/1 1; NITROGLYCERIN 12 [hp_X]/1 1; LACHESIS MUTA VENOM 30 [hp_X]/1 1; SULFUR 12 [hp_X]/1 1; ATROPA BELLADONNA 12 [hp_X]/1 1; CAULOPHYLLUM THALICTROIDES ROOT 12 [hp_X]/1 1; BLACK COHOSH 12 [hp_X]/1 1; NITROGLYCERIN 12 [hp_X]/1 1; STRYCHNOS IGNATII SEED 12 [hp_X]/1 1; LACHESIS MUTA VENOM 30 [hp_X]/1 1; ANEMONE PULSATILLA 12 [hp_X]/1 1; SEPIA OFFICINALIS JUICE 12 [hp_X]/1 1
INACTIVE INGREDIENTS: ACACIA; LACTOSE MONOHYDRATE; ACACIA; LACTOSE MONOHYDRATE

Doctor Wise Menopause+ Sleep

Drug Facts

Active ingredients

Active ingredients | Purpose
Belladonna 12X HPUS | hot flashes, night sweats
Caulophyllum 12X HPUS | irritability
Cimicifuga Racemosa 12X HPUS | hot flashes
Glonoinum 12X HPUS | occasional sleeplessness, restlessness
Ignatia Amara 12X HPUS | frequent waking, occasional sleeplessness, restlessness
Lachesis 30X HPUS | hot flashes
Pulsatilla 12X HPUS | hot flashes, night sweats
Sepia Officinalis 12X HPUS | irritability, hot flashes, night sweats
Sulphur 12X HPUS | hot flashes, night sweats

“HPUS” indicates that the active ingredients are in the official Homeopathic Pharmacopœia of the United States.

Uses

Temporarily relieves the symptoms of occasional sleeplessness, restlessness, frequent waking, irritability, hot flashes, and night sweats experienced during menopause.

Warnings

PREGNANCY OR BREAST FEEDING

As with any drug, ask a doctor before use if pregnant or breast-feeding.

Do not use:  • more than directed.  • if you have a known allergy to any ingredient in this product.

ASK DOCTOR

Consult a physician if symptoms persist for more than 7 days or worsen.

KEEP OUT OF REACH OF CHILDREN

Keep this and all medications out of reach of children. In case of accidental overdose, contact a medical professional or Poison Control Center immediately.

Do not use if imprinted tamper-evident bottle sleeve is broken or missing.

In case of emergency, contact a medical professional or Poison Control Center immediately. Doctor Wise by Hyland’s may also be contacted for emergency information about our products 24 hours a day, 7 days per week at (800) 624-9659.

Directions

Adults: Take two tablets at onset of symptoms and repeat every four hours as needed.

Inactive ingredients

Acacia Gum, Lactose

Questions or comments?

(800) 624-9659

Principal Display Panel - Doctor Wise Menopause+ Sleep

NDC 54973-3356-1

DOCTOR

WISE

HOMEOPATHY

MENOPAUSE+

SLEEP

Natural relief of occasional

sleeplessness, frequent waking,

hot flashes & night sweats*

SOY

FREE

68 SUBLINGUAL TABLETS

INCLUDES TWO 4-TABLETS SACHETS